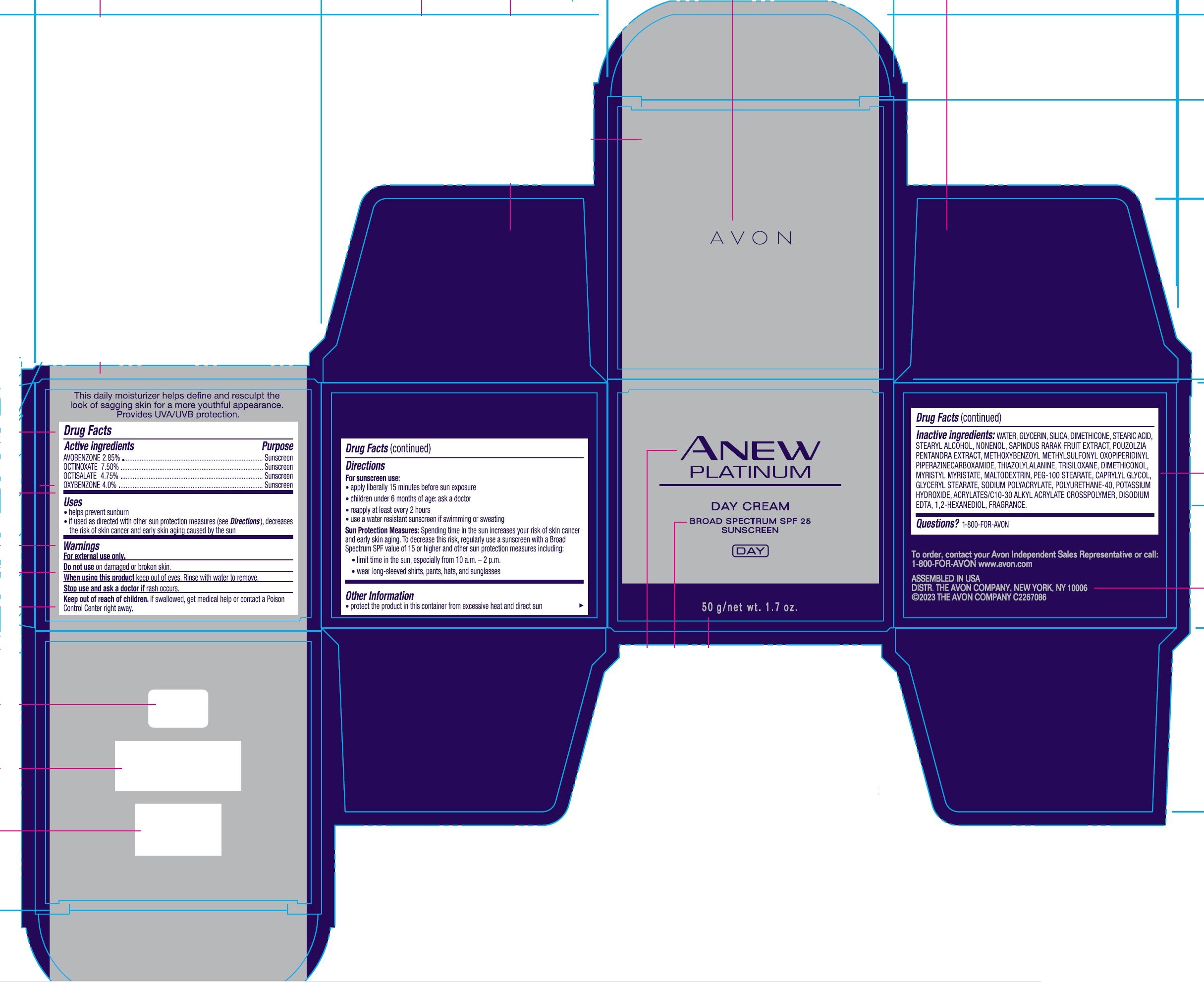 DRUG LABEL: Avon Anew Platinum Day-Cream SPF 25 Sunscreen
NDC: 10096-2550 | Form: CREAM
Manufacturer: The Avon Company
Category: otc | Type: HUMAN OTC DRUG LABEL
Date: 20240103

ACTIVE INGREDIENTS: OCTINOXATE 7.5 mg/1 g; OCTISALATE 4.75 mg/1 g; OXYBENZONE 4 mg/1 g; AVOBENZONE 2.85 mg/1 g
INACTIVE INGREDIENTS: WATER

Avon Anew Platinum Day Cream SPF 25 50g

Drug Facts

AVOBENZONE 2.85%
OCTINOXATE 7.5%
OCTISALATE 4.75%
OXYBENZONE 4.0%

Purpose

Sunscreen

Uses

- helps prevent sunburn
- if used as directed with other sun protection measures (see Directions), decrease the rist of skin cancer and early skin aging caused by the sun

Warnings

For external use only.

Do not use on damaged or broken skin.

When using this product keep out of eyes. Rinse with water to remove.

Stop use and ask a doctor if rash occurs.

Keep out of reach of children. If swallowed, get medical help or contact a Poison Control Center right away.

Directions

For sunscreen use:

- apply liberally 15 minutes before sun exposure
- children less than 6 months of age: ask a doctor
- reapply at least every 2 hours
- use a water resistant sunscreen if swimming or sweating

Sun Protection Measures: Spending time in the sun increases your risk of skin cancer and early skin aging. To decrease this risk, regularly use a sunscreen with a Broad Spectrum SPF value of 15 or higher and other sun protection measures including:

- limit time in the sun, especially from 10 a.m. – 2 p.m.
- wear long-sleeved shirts, pants, hats, and sunglasses

Other information

• protect the product in this container from excessive heat and direct sun

• the product may stain certain types of fabrics

Other information

- protect the product in this container from excessive heat and direct sun

Inactive Ingredients:

WATER, GLYCERIN, SILICA, DIMETHICONE, STEARIC ACID, STEARYL ALCOHOL, NONENOL, SAPINDUS RARAK FRUIT EXTRACT, POUZOLZIA PENTANDRA EXTRACT, METHOXYBENZOYL METHYLSULFONYL OXOPIPERIDINYL PIPERAZINECARBOXAMIDE, THIAZOLYLALANINE, TRISILOXANE, DIMETHICONOL, MYRISTYL MYRISTATE, MALTODEXTRIN, PEG-100 STEARATE, CAPRYLYL GLYCOL, GLYCERYL STEARATE, SODIUM POLYACRYLATE, POLYURETHANE-40, POTASSIUM HYDROXIDE, ACRYLATES/C10-30 ALKYL ACRYLATE CROSSPOLYMER, DISODIUM EDTA, 1,2-HEXANEDIOL, FRAGRANCE

Questions?

1-800-FOR-AVON

Principal Display Panel:

AVON
ANEW
PLATINUM
DAY CREAM
BROAD SPECTRUM SPF 25
SUNSCREEN
DAY
50 g/net wt. 1.7 oz.
This daily moisturizer helps define and resculpt the
look of sagging skin for a more youthful appearance.
Provides UVA/UVB protection.
To order, contact your Avon Independent Sales Representative or call:
1-800-FOR-AVON www.avon.com
ASSEMBLED IN USA
DISTR. THE AVON COMPANY, NEW YORK, NY 10006
©2023 THE AVON COMPANY C226708